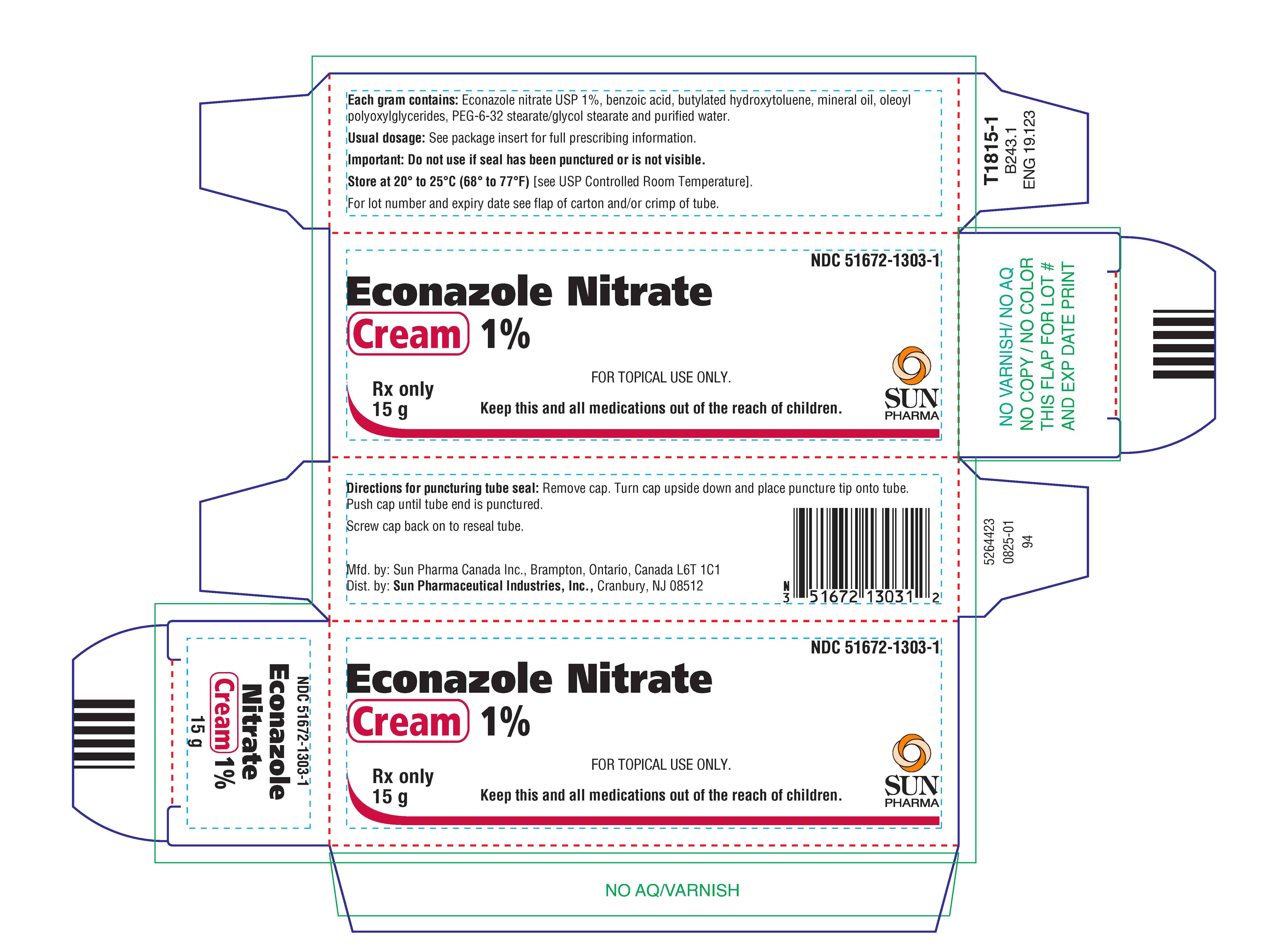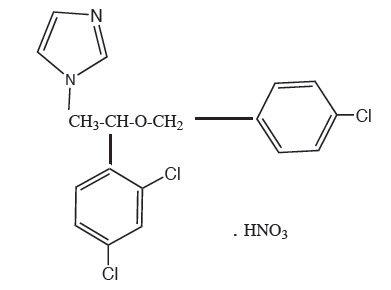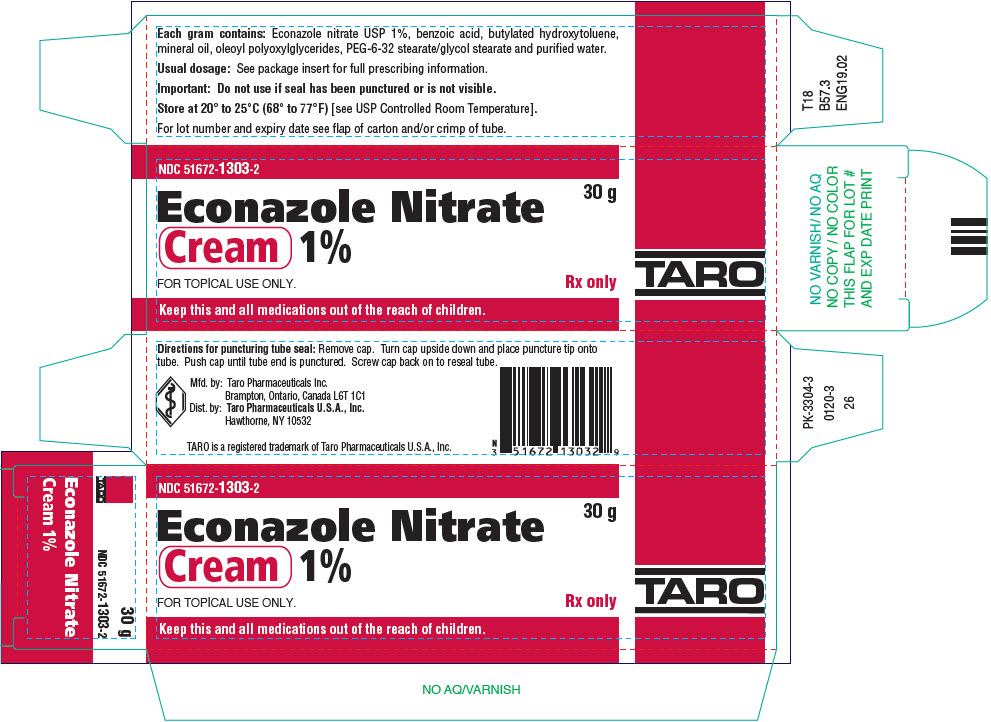 DRUG LABEL: Econazole Nitrate
NDC: 51672-1303 | Form: CREAM
Manufacturer: Sun Pharmaceutical Industries, Inc.
Category: prescription | Type: HUMAN PRESCRIPTION DRUG LABEL
Date: 20250826

ACTIVE INGREDIENTS: ECONAZOLE NITRATE 10 mg/1 g
INACTIVE INGREDIENTS: APRICOT KERNEL OIL PEG-6 ESTERS; BENZOIC ACID; BUTYLATED HYDROXYTOLUENE; MINERAL OIL; PEG-6 STEARATE; PEG-32 STEARATE; GLYCOL STEARATE; WATER

Econazole Nitrate
Cream 1%

For Topical Use Only

Rx Only

DESCRIPTION

Econazole nitrate cream contains the antifungal agent, econazole nitrate USP 1%, in a water-miscible base consisting of benzoic acid, butylated hydroxytoluene, mineral oil, oleoyl polyoxylglycerides PEG-6-32 stearate/glycol stearate and purified water. The white to off-white soft cream is for topical use only.

Chemically, econazole nitrate is 1-[2-{(4-chloro-phenyl) methoxy}-2-(2,4-dichlorophenyl)ethyl]-1H-imidazole mononitrate. Its structure is as follows:

CLINICAL PHARMACOLOGY

After topical application to the skin of normal subjects, systemic absorption of econazole nitrate is extremely low. Although most of the applied drug remains on the skin surface, drug concentrations were found in the stratum corneum, which, by far, exceeded the minimum inhibitory concentration for dermatophytes. Inhibitory concentrations were achieved in the epidermis and as deep as the middle region of the dermis. Less than 1% of the applied dose was recovered in the urine and feces.

Microbiology

Econazole nitrate has been shown to be active against most strains of the following microorganisms, both in vitroand in clinical infections as described in the INDICATIONS AND USAGE section.

Dermatophytes

Yeasts

Epidermophyton floccosum

Candida albicans

Microsporum audouini

Malassezia furfur

Microsporum canis

Microsporum gypseum

Trichophyton mentagrophytes

Trichophyton rubrum

Trichophyton tonsurans

Econazole nitrate exhibits broad-spectrum antifungal activity against the following organisms in vitro, but the clinical significance of these data is unknown.

Dermatophytes | Yeasts
Trichophyton verrucosum | Candida guillermondii
 | Candida parapsilosis
 | Candida tropicalis

INDICATIONS AND USAGE

Econazole nitrate cream is indicated for topical application in the treatment of tinea pedis, tinea cruris, and tinea corporis caused by Trichophyton rubrum, Trichophyton mentagrophytes, Trichophyton tonsurans, Microsporum canis, Microsporum audouini, Microsporum gypseum,and Epidermophyton floccosum,in the treatment of cutaneous candidiasis, and in the treatment of tinea versicolor.

CONTRAINDICATIONS

Econazole nitrate cream is contraindicated in individuals who have shown hypersensitivity to any of its ingredients.

WARNINGS

Econazole nitrate cream is not for ophthalmic use.

PRECAUTIONS

General

If a reaction suggesting sensitivity or chemical irritation should occur, use of the medication should be discontinued.

For external use only. Avoid introduction of econazole nitrate cream into the eyes.

Drug Interactions

Warfarin

Concomitant administration of econazole and warfarin has resulted in enhancement of anticoagulation effect. Most cases reported product application with use under occlusion, genital application, or application to large body surface area which may increase the systemic absorption of econazole nitrate. Monitoring of International Normalized Ratio (INR) and/or prothrombin time may be indicated especially for patients who apply econazole to large body surface areas, in the genital area, or under occlusion.

Carcinogenesis, mutagenesis, impairment of fertility

Long-term animal studies to determine carcinogenic potential have not been performed.

Oral administration of econazole nitrate in rats has been reported to produce prolonged gestation. Intravaginal administration in humans has not shown prolonged gestation or other adverse reproductive effects attributable to econazole nitrate therapy.

Pregnancy

Econazole nitrate has not been shown to be teratogenic when administered orally to mice, rabbits or rats. Fetotoxic or embryotoxic effects were observed in Segment I oral studies with rats receiving 10 to 40 times the human dermal dose. Similar effects were observed in Segment II or Segment III studies with mice, rabbits and/or rats receiving oral doses 80 or 40 times the human dermal dose.

Econazole nitrate should be used in the first trimester of pregnancy only when the physician considers it essential to the welfare of the patient. The drug should be used during the second and third trimesters of pregnancy only if clearly needed.

Nursing Mothers

It is not known whether econazole nitrate is excreted in human milk. Following oral administration of econazole nitrate to lactating rats, econazole and/or metabolites were excreted in milk and were found in nursing pups. Also, in lactating rats receiving large oral doses (40 or 80 times the human dermal dose), there was a reduction in post partum viability of pups and survival to weaning; however, at these high doses, maternal toxicity was present and may have been a contributing factor. Caution should be exercised when econazole nitrate is administered to a nursing woman.

Geriatric Use

Clinical studies of econazole nitrate cream did not include sufficient numbers of subjects aged 65 and over to determine whether they respond differently from younger subjects. Other reported clinical experience has not identified differences in responses between the elderly and younger patients. In general, dose selection for an elderly patient should be cautious, usually starting at the low end of the dosing range, reflecting the greater frequency of decreased hepatic, renal, or cardiac function, and of concomitant disease or other drug therapy.

ADVERSE REACTIONS

During clinical trials, approximately 3% of patients treated with econazole nitrate cream 1% reported side effects thought possibly to be due to the drug, consisting mainly of burning, itching, stinging and erythema. One case of pruritic rash has also been reported.

OVERDOSE

Overdosage of econazole nitrate in humans has not been reported to date. In mice, rats, guinea pigs and dogs, the oral LD 50 values were found to be 462, 668, 272, and >160 mg/kg, respectively.

DOSAGE AND ADMINISTRATION

Sufficient econazole nitrate cream, 1%, should be applied to cover affected areas once daily in patients with tinea pedis, tinea cruris, tinea corporis, and tinea versicolor, and twice daily (morning and evening) in patients with cutaneous candidiasis.

Early relief of symptoms is experienced by the majority of patients and clinical improvement may be seen fairly soon after treatment is begun; however, candidal infections and tinea cruris and corporis should be treated for two weeks and tinea pedis for one month in order to reduce the possibility of recurrence. If a patient shows no clinical improvement after the treatment period, the diagnosis should be redetermined. Patients with tinea versicolor usually exhibit clinical and mycological clearing after two weeks of treatment.

HOW SUPPLIED

Econazole Nitrate Cream, 1% is supplied in tubes of 15 g (NDC 51672-1303-1), 30 g (NDC 51672-1303-2) and 85 g (NDC 51672-1303-8).

STORAGE AND HANDLING

Store at 20° to 25°C (68° to 77°F) [see USP Controlled Room Temperature].

To report SUSPECTED ADVERSE REACTIONS, contact Sun Pharmaceutical Industries, Inc., at 1-866-923-4914 or FDA at 1-800-FDA-1088 or www.fda.gov/medwatch for voluntary reporting of adverse reactions.

Mfd. by: Sun Pharma Canada Inc., Brampton, Ontario, Canada L6T 1C1
Dist. by: Sun Pharmaceutical Industries, Inc., Cranbury, NJ 08512

Revised: August 2025 5264354-0825-01

PRINCIPAL DISPLAY PANEL - 30 g Tube Carton

.